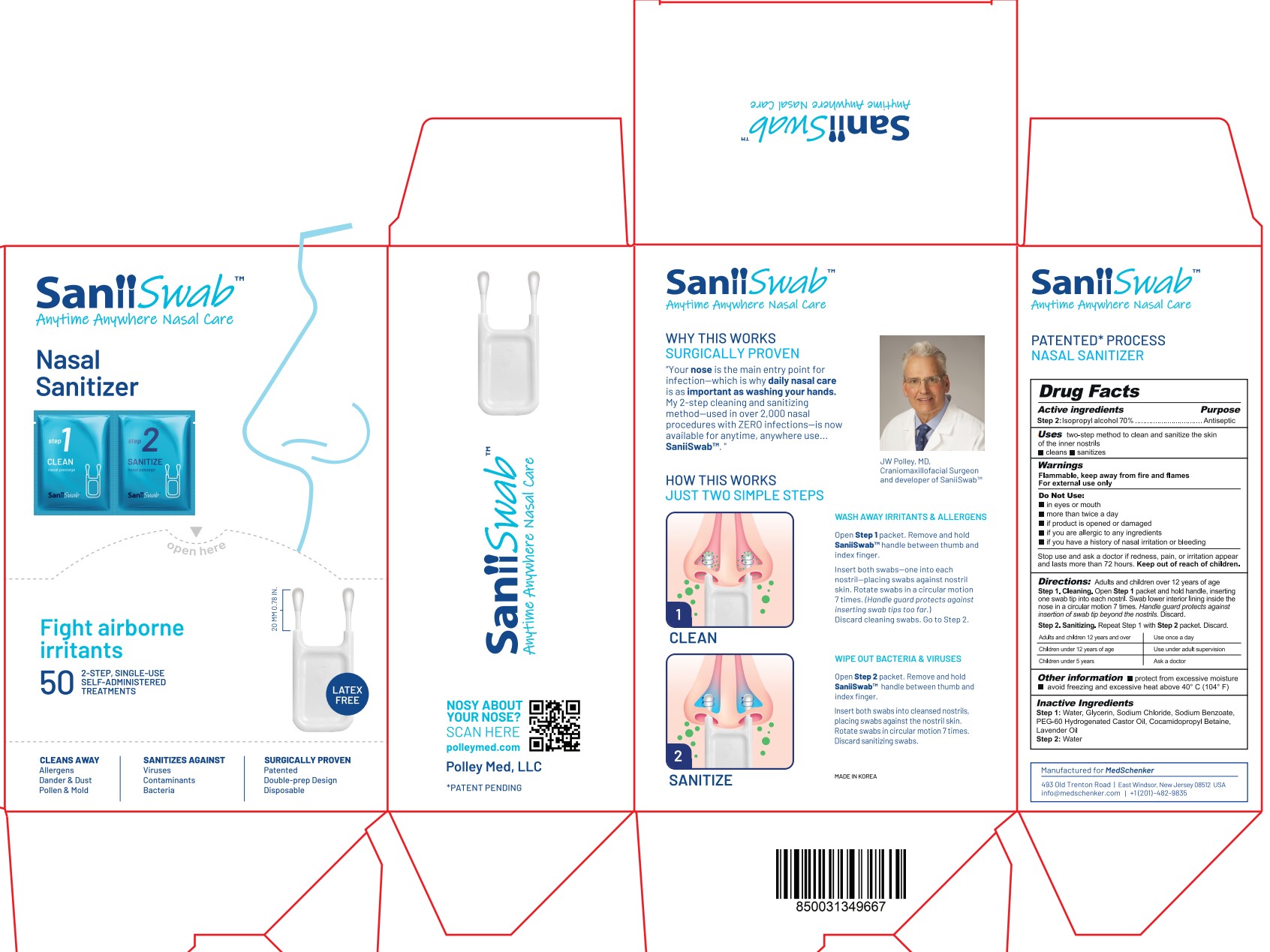 DRUG LABEL: SaniiSwab
NDC: 77039-026 | Form: LIQUID
Manufacturer: IDO PHARM
Category: otc | Type: HUMAN OTC DRUG LABEL
Date: 20230920

ACTIVE INGREDIENTS: ISOPROPYL ALCOHOL 70 mL/100 g
INACTIVE INGREDIENTS: WATER

ACTIVE INGREDIENT

isopropyl alcohol 70%

INACTIVE INGREDIENT

Water

PURPOSE

two-step method to clean and sanitize the skin of the inner nostrils

■ cleans ■ sanitizes

Keep out of reach of children

INDICATIONS AND USAGE

Adults and children over 12 years of age
Step 1. Cleaning. Open Step 1 packet and hold handle, inserting
one swab tip into each nostril. Swab lower interior lining inside the
nose in a circular motion 7 times. Handle guard protects against
insertion of swab tip beyond the nostrils. Discard.
Step 2. Sanitizing. Repeat Step 1 with Step 2 packet. Discard

WARNINGS

Flammable, keep away from fire and flames
For external use only

DOSAGE AND ADMINISTRATION

For external use only